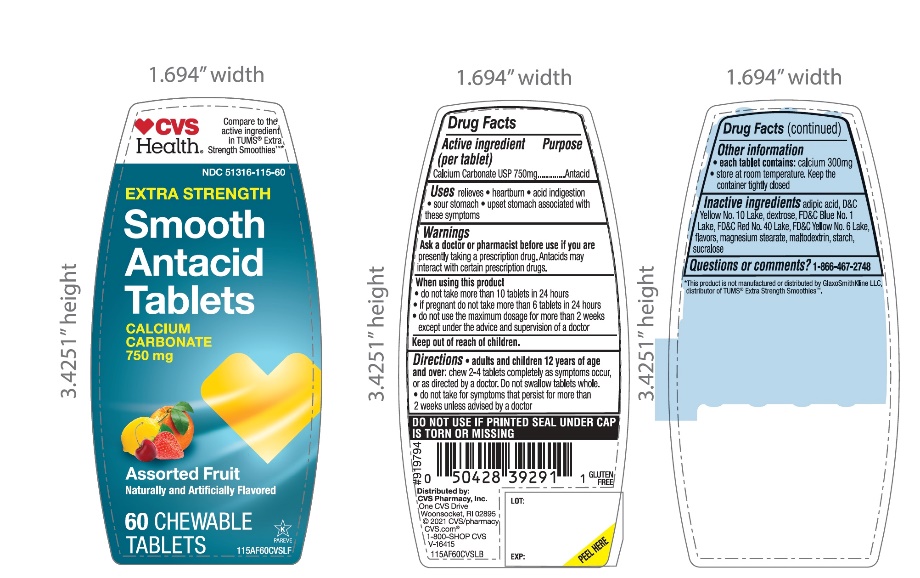 DRUG LABEL: Extra Strength Smooth
NDC: 51316-115 | Form: TABLET, CHEWABLE
Manufacturer: CVS
Category: otc | Type: HUMAN OTC DRUG LABEL
Date: 20251208

ACTIVE INGREDIENTS: CALCIUM CARBONATE 750 mg/1 1
INACTIVE INGREDIENTS: ADIPIC ACID; D&C YELLOW NO. 10; DEXTROSE, UNSPECIFIED FORM; FD&C BLUE NO. 1; FD&C RED NO. 40; FD&C YELLOW NO. 6; MAGNESIUM STEARATE; MALTODEXTRIN; STARCH, CORN; SUCRALOSE

CVS Extra Strength Smooth Antacid Tablets

Active ingredient

Calcium Carbonate USP 750mg

Purpose

Antacid

Uses

relieves:

• heartburn

• sour stomach

• acid indigestion

• upset stomach associated with these symptoms

Warnings

Ask a doctor or pharmacist before use if you aretaking a prescription drug. Antacids may interact with certain prescription drugs.

When using this product

• do not take more than 10 tablets in 24 hours

• if pregnant do not take more than 6 tablets in 24 hours

• do not use the maximum dosage for more than 2 weeks except under the advice and supervision of a doctor

Directions

• adults and children 12 years of age and over:chew 2-4 tablets completely as symptoms occur, or as directed by a doctor. Do not swallow tablets whole.

• do not take for symptoms that persist for more than 2 weeks unless advised by a doctor.

Other Information

• each tablet contains:calcium 300mg

• Store at room temperature. Keep the container tightly closed

Inactive ingredients

adipic acid, D&C Yellow No. 10 Lake, dextrose, FD&C Blue No. 1 Lake, FD&C Red No. 40 Lake, FD&C Yellow No. 6 lake, flavors, magnesium stearate, maltodextrin, starch, sucralose

Safety sealed: Do not use if printed seal under cap is torn or missing

Questions or comments?

1-866-467-2748

Package/Label Principal Display Panel

*Compare to the active ingredient in Extra Strength Tums®Smoothies™

EXTRA STRENGTH

Smooth Antacid Tablets

Calcium Carbonate 750 mg

For Fast Relief of Heartburn, Acid Indigestion & Upset Stomach

Assorted Fruit

Naturally and Artificially Flavored

60 Chewable Tablets

Distributed by:

*This product is not manufactured or distributed by GlaxoSmithKline, owner of the registered trademark, Extra Strength Tums® Smoothies™